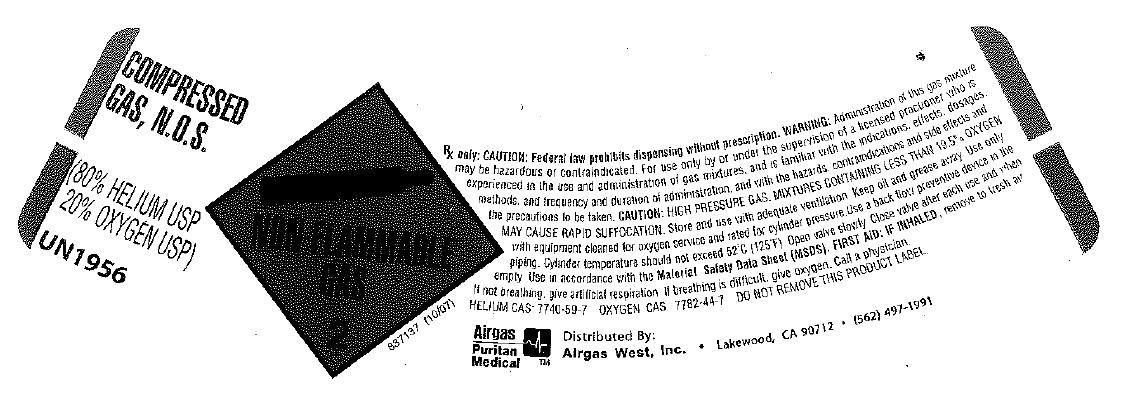 DRUG LABEL: Helium Oxygen Mix 80/20
NDC: 10678-011 | Form: GAS
Manufacturer: Airgas-West, Inc.
Category: prescription | Type: HUMAN PRESCRIPTION DRUG LABEL
Date: 20100527

ACTIVE INGREDIENTS: Helium 800 mL/1 L; Oxygen 200 mL/1 L

He O2 mix 80/20

PACKAGE LABEL

COMPRESSED GAS, N.O.S.
(80% HELIUM USP, 20% OXYGEN USP)
UN1956
NON-FLAMMABLE 2
837137 (10/07)
Rx only.CAUTION: Federal law prohibits dispensing without a prescription. WARNING: Administration of this gas mixture may be hazardous or contraindicated. For use by or under the supervision of a licensed practitioner who is experienced in the use and administration of gas mixtures, and is familiar with the indications, effects, dosages, methods, and frequency and duration of administration, and with the hazards, contraindications and side effects, and the precautions to be taken.
CAUTION: HIGH PRESSURE GAS. MIXTURES CONTAINING LESS THAN 19.5% OXYGEN MAY CAUSE RAPID SUFFOCATION. Store and use with adequate ventilation. Keep oil and grease away. Use only with equipment cleaned for oxygen service and rated for cylinder pressure. Use a back flow preventive device in the piping. Cylinder temperature should not exceed 52oC(125oF). Open valve slowly. Close valve after each use and when empty. Use in accordance with the Material Safety Data Sheet (MSDS).
FIRST AID: IF INHALED, remove to fresh air. If not breathing, give artificial respiration. If breathing is difficult, give oxygen. Call a physician. HELIUM CAS: 7440-59-7 OXYGEN CAS: 7782-44-7
DO NOT REMOVE THIS PRODUCT LABEL.
AIRGAS PURITAN MEDICAL Distributed By: Airgas West, Inc. Lakewood, CA 90712 (562) 497-1991